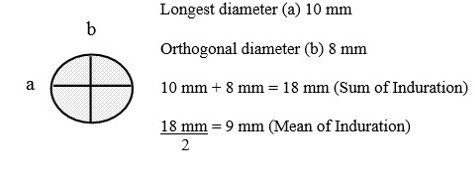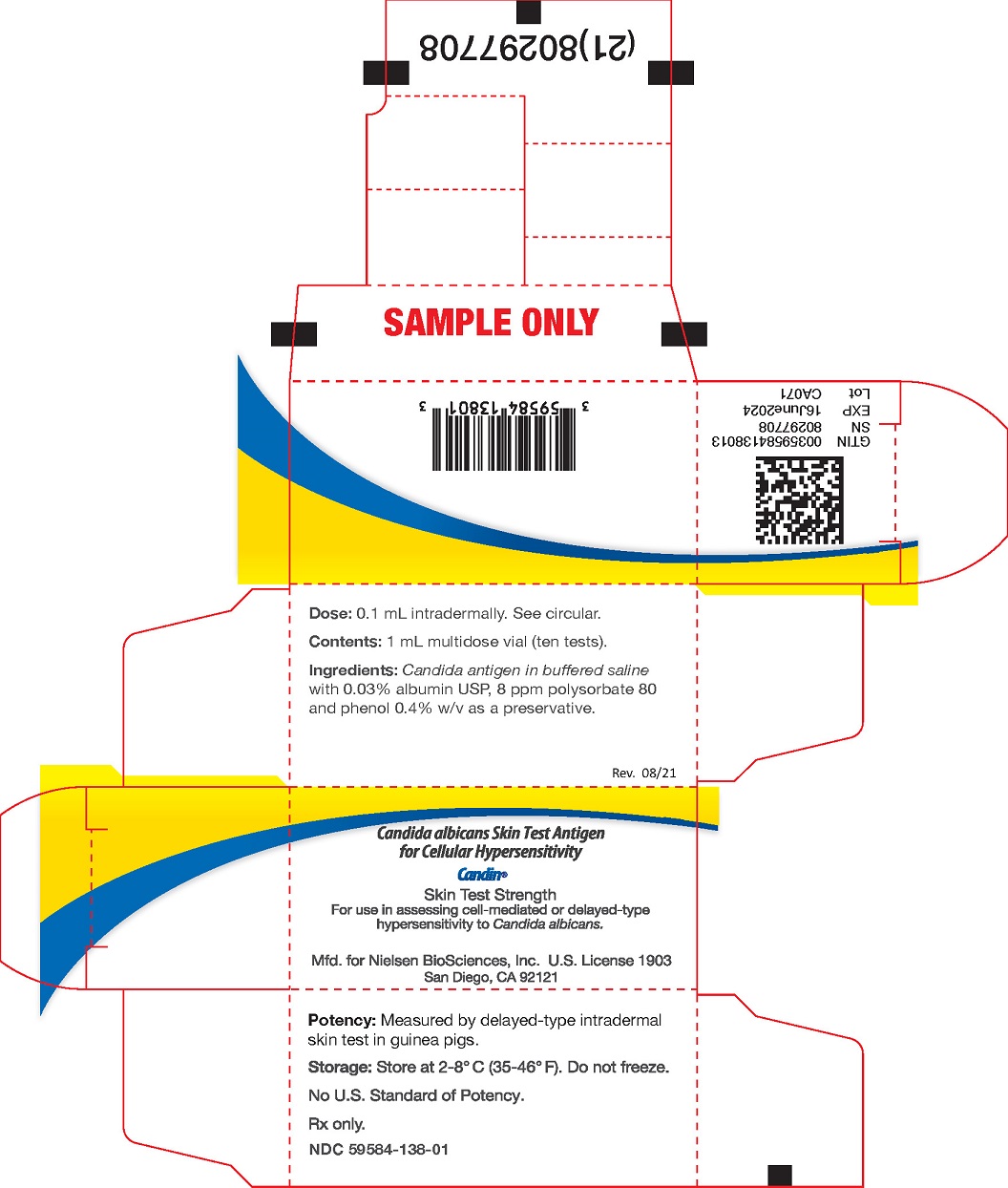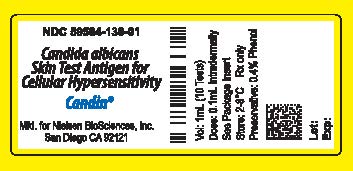 DRUG LABEL: Candin
NDC: 59584-138 | Form: INJECTION, SOLUTION
Manufacturer: Nielsen BioSciences, Inc.
Category: other | Type: STANDARDIZED ALLERGENIC
Date: 20250114

ACTIVE INGREDIENTS: CANDIDA ALBICANS 1 U/0.1 mL
INACTIVE INGREDIENTS: ALBUMIN HUMAN 0.03 mg/0.1 mL; SODIUM CHLORIDE 0.5 mg/0.1 mL; SODIUM BICARBONATE 0.25 mg/0.1 mL; POLYSORBATE 80 0.8 ug/0.1 mL; PHENOL 0.4 mg/0.1 mL; WATER

HIGHLIGHTS OF PRESCRIBING INFORMATION

These highlights do not include all the information needed to use CANDIN® safely and effectively. See full prescribing information for CANDIN®.
Candida albicans Skin Test Antigen For Cellular Hypersensitivity
CANDIN intradermal injection
Initial U.S. Approval: 1995

WARNING

See full prescribing information for complete boxed warning.

- The expected response to CANDIN® is a local area of inflammation at the site of the skin test. The reaction is usually dime to quarter size reaching maximum diameter between 24 and 48 hours. Larger accelerated reactions can occur, which may require treatment with local cold compresses and anti-inflammatory medication. (2.3, 6.1)
- Systemic reactions can occur with skin test antigens and in certain individuals these reactions may be life-threatening or cause death. Emergency measures and personnel trained in their use should be immediately available. Patients should be observed for at least 20 minutes following the administration of a skin test. (6.2)
- CANDIN® should never be given intravenously. (5)
- To report SUSPECTED ADVERSE REACTIONS contact Nielsen BioSciences, Inc. at (855) 855-1212 or MEDWATCH, Food and Drug Administration, 5600 Fishers Lane, Rockville, MD 20852-9782. Telephone (800) 332-1088 or www.vaers.hhs.gov. (6.3)

1 INDICATIONS AND USAGE

- CANDIN® is a skin test antigen to assess cellular hypersensitivity to Candida albicans.
- The product should not be used to diagnose or treat Type 1 allergy to Candida albicans.

2 DOSAGE AND ADMINISTRATION

- CANDIN® skin test dose is 0.1 mL administered intradermally. (2.1)

3 DOSAGE FORMS AND STRENGTHS

- CANDIN® is a solution for intradermal injection supplied in a 1 mL multi-dose vial. (3.1)
- The skin-test strength of CANDIN® is determined from dose-response studies in in healthy adults. The product is intended to elicit an induration response ≥5 mm in immunologically competent persons with cellular hypersensitivity to the antigen (see DOSAGE AND ADMINISTRATION). (3.2)

4 CONTRAINDICATIONS

- CANDIN® should not be used after a previous unacceptable adverse reaction to this antigen or to a similar product, i.e., extreme hypersensitivity/allergy. (4.0)

5 WARNINGS AND PRECAUTIONS

- The antigen must be injected intradermally. Do not inject intravenously. (5.1)
- As has been observed with unstandardized antigens used for DTH skin testing, it is possible that some patients may have exquisite immediate hypersensitivity to CANDIN®. (5.2)
- Physicians using this product must have facilities, equipment and medication necessary to treat potential side effects. Epinephrine and oxygen must be immediately available in the event of a serious systemic response. (5.3)

6 ADVERSE REACTIONS

- Immediate hypersensitivity local reactions can include itching, swelling, pain and blistering at the test site occurring 15-20 minutes after administration. Necrosis is possible. (6.1)
- Systemic reactions to CANDIN® have not been observed, however all foreign antigens have the remote possibility of causing Type 1 anaphylaxis and even death when injected intradermally. (6.2)
- To report SUSPECTED ADVERSE REACTIONS contact Nielsen BioSciences, Inc. at (855) 855-1212 or MEDWATCH, Food and Drug Administration, 5600 Fishers Lane, Rockville, MD 20852-9782. Telephone 1-800-332-1088 or https://www.vaers.hhs.gov/. (6.3)

7 DRUG INTERACTIONS

- Corticosteroids and immunosuppressive drugs
- Beta-blocking drugs. (7.0)

8 USE IN SPECIFIC POPULATIONS

- Use in pediatric populations has not been established.
- Geriatric populations may have a diminished response to the skin test. (8.5)

FULL PRESCRIBING INFORMATION

WARNING

See full prescribing information for complete boxed warning.

- The expected response to CANDIN® is a local area of inflammation at the site of the skin test. The size of reaction depends upon the sensitivity of the person receiving the test, but is usually dime to quarter size reaching maximum diameter between 24 and 48 hours. Larger accelerated reactions can occur which may require treatment with local cold compresses and anti-inflammatory medication. (2.3, 6.1)
- Systemic reactions can occur with skin test antigens and in certain individuals these reactions may be life-threatening or cause death. Emergency measures as well as personnel trained in their use should be immediately available in the event of a life-threatening reaction. Patients should be observed for at least 20 minutes following the administration of a skin test. (6.2)
- CANDIN® should never be given intravenously. See also Warnings and Precautions. (5.1)
- Serious adverse reactions to CANDIN® should be reported to Nielsen BioSciences, Inc. at (855) 855-1212 or MEDWATCH, Food and Drug Administration, 5600 Fishers Lane, Rockville, MD 20852-9782. Telephone: (800) 332-1088 or www.vaers.hhs.gov. (6.3)

1 INDICATIONS AND USAGE

CANDIN® is indicated for use as a recall antigen for detecting cell-mediated hypersensitivity by intracutaneous (intradermal) testing. The product may be useful in evaluating the cellular immune response in patients suspected of having reduced cellular hypersensitivity. Because some persons with normal cellular immunity are not hypersensitive to Candida, a response rate less than 100% to the antigen is to be expected in normal individuals. Therefore, the concurrent use of other licensed cell-mediated hypersensitivity skin test antigens is recommended. The product should not be used to diagnose or treat Type 1 allergy to Candida albicans.

2 DOSAGE AND ADMINISTRATION

2.1 Dosage

Parenteral drug products should be inspected visually for particulate matter and discoloration prior to administration, whenever solution and container permit. If particles or discoloration are observed, the product should not be used and it should be discarded.

2.2 Administration

CANDIN® should be administered intradermally on the volar surface of the forearm or on the outer aspect of the upper arm. The test dose is 0.1 mL. The skin should be cleansed with 70% alcohol before applying the skin test. The intradermal injection must be given as superficially as possible causing a distinct, sharply defined bleb. An unreliable reaction may result if the product is injected subcutaneously. A positive DTH reaction to CANDIN® consists of induration ≥ 5 mm.

2.3 Reading the Skin Test Result

The time required for the induration response to reach maximum intensity varies with the individual. The reaction usually begins within 24 hours and peaks between 24 and 48 hours. The skin test should be read at 48 hours by visually inspecting the test site and palpating the indurated area. Measurements should be made across two diameters as shown in the figure below. The mean of the longest and midpoint orthogonal diameters of the indurated area should be reported as the DTH response. For example, a reaction that is 10 mm (longest diameter) by 8 mm (midpoint orthogonal diameter) has a sum of 18 mm and a mean of 9 mm. The DTH response is therefore 9 mm.

Area of Induration

(shaded area)

3 DOSAGE FORMS AND STRENGTHS

3.1 Dosage Form

CANDIN® is a solution for intradermal injection supplied in a 1 mL multi-dose vial.

3.2 Skin Test Strength

The skin-test strength of CANDIN® has been determined from dose-response studies in healthy adults (see CLINICAL STUDIES). The product is intended to elicit an induration response ≥5 mm in immunologically competent persons with cellular hypersensitivity to the antigen (see DOSAGE AND ADMINISTRATION).

4 CONTRAINDICATIONS

CANDIN® should not be used after a previous unacceptable adverse reaction to this antigen or to a similar product, i.e., extreme hypersensitivity/allergy.

5 WARNINGS AND PRECAUTIONS

5.1 Administer Intracutaneously, Not Intravenously

The antigen must be injected intradermally as superficially as possible, causing a distinct, sharply defined bleb at the skin test site. An unreliable reaction may result if the product is injected subcutaneously. It must not be given intravenously; care should be taken to avoid injection into a blood vessel. A separate sterile syringe and needle should be used for each patient to prevent transmission of infectious agents. Needles should be disposed of properly and should not be recapped.

5.2 In Persons with Bleeding Tendency, Bruising and Non-Specific Induration May Occur Due to the Trauma of the Skin Test

It is possible that some patients may have exquisite immediate hypersensitivity to CANDIN®. In persons with bleeding tendency, bruising and non-specific induration may occur due to the trauma of the skin test. As with all skin test antigens, local and systemic allergic reactions can occur following administration.

5.3 Access to Emergency Equipment, Medications

Physicians using this product must have facilities, equipment and medication necessary to treat potential side effects. Epinephrine and oxygen must be immediately available in the event of a serious systemic response.

6 ADVERSE REACTIONS

6.1 Local Reactions

Local reactions to CANDIN® have included swelling, pruritus and vesiculation. Reactions involving necrosis and ulceration have not been observed, but such reactions are theoretically possible and might occur in persons with exquisite cellular hypersensitivity to the antigen. Local reactions may be treated with a cold compress and topical steroids.

Severe local reactions, including rash, vesiculation, bullae, dermal exfoliation and cellulitis are possible in highly allergic persons. Severe local reactions may require additional measures as appropriate. In a published study of 479 HIV positive adults tested with CANDIN®, adverse local reactions were observed in six subjects as follows: pruritus (three), swelling at the test site (one), vesiculation (one) and vesiculation with weeping edema (one). Pruritus and swelling cleared within 48 hours; vesiculation with edema required approximately 1 week to resolve.(6)

In two studies involving 171 persons discussed under CLINICAL STUDIES in Tables 1, 2, 3, and text, one adverse reaction was observed. This reaction consisted of induration 22 x 55 mm at 48 hours which resolved within 1 week .

Local immediate hypersensitivity reactions to CANDIN® occur in some individuals. These reactions are characterized by the presence of an edematous hive surrounded by a zone of erythema. They occur approximately 15 - 20 minutes after the intradermal injection of the antigen. The size of the immediate reaction varies depending upon the sensitivity of the individual. Local immediate hypersensitivity reactions were observed in the control and HIV-infected (AIDS and HIV positive) subjects reported in Table 2 as follows: HIV-infected subjects (20% with erythema of 10 - 21 mm in diameter; 13% with erythema of 5 - 9 mm). Control subjects (22% with erythema of 10 - 15 mm; 5% with erythema of 8.5 mm). Cancer subjects (Group 1, Table 3), 17% with erythema of 10 - 24 mm and 11% with erythema of 6 - 9 mm.

6.2 Systemic Reactions

Systemic reactions to CANDIN® have not been observed. However, all foreign antigens have the remote possibility of causing Type 1 anaphylaxis and even death when injected intradermally.(7) Systemic reactions usually occur within 30 minutes after the injection of antigen and may include the following symptoms: sneezing, coughing, itching, shortness of breath, abdominal cramps, vomiting, diarrhea, tachycardia, hypotension and respiratory failure in severe cases. Systemic allergic reactions including anaphylaxis must be immediately treated with Epinephrine HCL 1:1,000. Additional measures may be required, depending upon the severity of the reaction.

6.3 Reporting Suspected Adverse Events

To report SUSPECTED ADVERSE REACTIONS, contact Nielsen BioSciences, Inc. at (855) 855-1212 or MEDWATCH, Food and Drug Administration, 5600 Fishers Lane, Rockville, MD 20852-9782. Telephone 1-800-332-1088 or https://www.vaers.hhs.gov/.

7 DRUG INTERACTIONS

7.1 Corticosteroids and Imunosuppressive Drugs

Pharmacologic doses of corticosteroids may variably suppress the DTH skin test response after two weeks of therapy. The mechanism of suppression is believed to involve a decrease in monocytes and lymphocytes, particularly T-cells. The skin test response usually returns to the pretreatment level within several weeks after steroid therapy is discontinued.(1)

7.2 Beta-Blocking Drugs

Patients receiving beta-blocking drugs may be refractive to the usual dose of epinephrine, in the event that epinephrine is required to control an adverse allergic reaction.(1)

8 USE IN SPECIFIC POPULATIONS

8.1 Pregnancy

TERATOGENIC EFFECTS

Animal reproduction studies have not been conducted with CANDIN®. It is also not known whether CANDIN® can cause fetal harm when administered to a pregnant woman or can affect reproduction capacity. CANDIN® should be given to pregnant women only if clearly needed.

8.2 Labor and Delivery

No information is available to assess the effects of CANDIN® on childbirth.

8.3 Nursing Mothers

It is not known whether CANDIN® is excreted in human milk. Because drugs may be excreted in human milk, caution should be exercised when this product is administered to a nursing woman.

8.4 Pediatric Use

The safety and effectiveness of intradermally administered CANDIN® have not been established in children.

8.5 Geriatric Use

CANDIN® has not been adequately studied in geriatric patients. However, the DTH response to CANDIN® may be diminished in geriatric patients, since the aging process is known to alter cell-mediated immunity. (1)

10 OVERDOSAGE

The recommended dose for CANDIN® is 0.1 mL administered intradermally. If a larger dose is administered, or if the dose is accidentally injected intravenously, the potential for a systemic reaction such as anaphylaxis is increased. In this case, Epinephrine HCl at 1:1000 should be made available immediately as well as oxygen and emergency equipment.

Because individuals differ in their sensitivity to CANDIN®, the response to the recommended dose of 0.1 mL can vary in size and intensity. In highly sensitive persons, the result of overdose, or a mistake in the administration of CANDIN® may result in a more pronounced local or systemic outcome.

11 DESCRIPTION

Candida albicans Skin Test Antigen for Cellular Hypersensitivity (CANDIN®) is a clear, colorless, sterile solution with a pH of 7.0 - 8.5. The antigen should be administered intradermally according to the directions included under DOSAGE AND ADMINISTRATION of this package insert.

CANDIN® is made from the culture filtrate and cells of two strains of Candida albicans. The fungi are propagated in a chemically defined medium consisting of inorganic salts, biotin and sucrose. Lyophilized source material is extracted with a solution of 0.25% NaCl, 0.125% NaHCO3 and 50% v/v glycerol. The concentrated extract is diluted with a solution of 0.5% NaCl, 0.25% NaHCO3, 0.03% Albumin (Human) USP, 8 ppm polysorbate 80 and 0.4% phenol.

The potency of CANDIN® is measured by DTH skin tests using a validated assay measuring relative potency in Guinea pigs based on induration responses at different dilutions against an Internal Reference standard.

12 CLINICAL PHARMACOLOGY

12.1 Mechanism of Action

Cellular hypersensitivity or delayed-type hypersensitivity (DTH) can be assessed by intracutaneous testing with bacterial, viral and fungal antigens to which most healthy persons are sensitized. A positive skin test denotes prior antigenic exposure, T-cell competency and an intact inflammatory response. (1, 2) The reaction usually peaks between 24 and 48 hours after antigen is introduced into the skin and is manifest as induration at the test site.

12.2 Pharmacodynamics

The inflammatory response associated with the DTH reaction is characterized by an infiltration of lymphocytes and macrophages at the site of antigen deposition. Specific cell types that appear to play a major role in the DTH response include CD4+ and CD8+ T lymphocytes which leave the recirculating lymphocyte pool in response to exogenous antigen. (3) Both CD4+ and CD8+ lymphocytes have been recovered from DTH reactions elicited by Candida antigen. (4)

13 NONCLINICAL TOXICOLOGY

13.1 Carcinogenesis, Mutagenesis, Impairment of Fertility

Long-term studies in animals have not been conducted with CANDIN® to determine its potential for carcinogenicity, mutagenicity or impairment of fertility.

14 CLINICAL STUDIES

14.1 Cellular Hypersensitivity Response to CANDIN® in Healthy Adults

In one group of 18 subjects, 14 (78%) of the individuals reacted to CANDIN® with an induration response of ≥ 5 mm at 48 hours. In a second study of 35 subjects, 21 (60%) had induration reactions ≥ 5 mm at 48 hours. In this study, 65% of males tested positive compared to 53% of females; the mean induration in responding males was 12.8 mm and in responding females was 13.0 mm.

Table 1. Induration response to CANDIN in healthy adults.

 | n | Age range (years) | Number reactions ≥ 5 mm at 48 hrs | Combined male/female Response
Study 1 (a)
Male | 16 | 25 – 83 | 12 | 78%
Female | 2 | 61 – 69 | 2 | 78%
Study 2
Male | 20 | 23 – 63 | 13 | 60%
Female | 15 | 28 – 62 | 8 | 60%

(a) Control group in Table 2.

14.2 Response to CANDIN® in Adults with HIV Infection

Response to CANDIN® in Adults with HIV Infection: In one study (Table 2), the skin test responses of adults with HIV infection were compared to those of healthy control subjects (age range AIDS 22 - 65, HIV positive 20 - 45, Controls 25 - 69). When HIV-infected subjects were classified by the CDC's 1993 revised classification system for HIV infection (5), a significant difference was found between AIDS patients and normal controls in both mean induration (p = 0.01) and proportion with ≥ 5 mm response (p < 0.01). The responses in HIV-infected patients (without AIDS-indicating conditions or AIDS-indicating CD4 T-cell counts) were less than in normal subjects, but the differences were not statistically significant.

In a second study involving 20 male patients (age range 26 - 57) diagnosed with AIDS based on clinical criteria only, one subject responded to CANDIN®. In the same study 65% of the male control subjects had DTH reactions ≥ 5 mm to CANDIN® (Table 1, Study 2). The mean induration response at 48 hours for control subjects was 8.33 mm compared to 1.78 mm for the AIDS subject. AIDS vs. control p-values were < 0.01 mean induration and < 0.01 induration ≥ 5 mm.

Because HIV infection can modify the DTH response to tuberculin, it is advisable to skin test HIV-infected patients at high risk of tuberculosis with antigens in addition to tuberculin.(6) In a published study of DTH anergy, 479 subjects (334 males and 145 females) infected with HIV and being screened for tuberculosis were skin tested with several additional antigens, including CANDIN® supplied under IND to the investigators. Only 12% reacted to tuberculin (≥ 5 mm), 57% reacted to CANDIN® (≥ 3 mm) and 60% reacted to either tuberculin or CANDIN® or both. In this study, a 3 mm induration response to CANDIN® was considered positive. The authors concluded that in HIV-infected subjects, testing with other DTH antigens increases the accuracy of interpretation of negative tuberculin reactions.

Table 2. Cellular hypersensitivity response to CANDIN® in adults with AIDS, adults with HIV infection (no-AIDS-indicator conditions) and adult control subjects. Range and mean of CD4 T-cell count shown in the shaded area of the table.

Group | Classifi- cation* | n | Zidovu- dine Use | CD4; Range | CD4; Mean | Mean Indur. (mm) | n≥5 mm | %
AIDS | A3,B3,C | 32 | 14 | 4-483 | 145 | 3.35(a) | 9 | 28(b)
HIV Pos. | A1,A2, B1,B2 | 28 | 13 | 201-1065 | 455 | 5.67 | 15 | 54
Control† | ------ | 18 | 0 | 554-1876 | 869 | 8.03 | 14 | 78

* (reference 5)
(a) p = 0.01 compared to Control. (b) p < 0.01 compared to Control.
† See Control Group in Table 1.

14.3 Response to CANDIN® in Adults with Cancer

In one study of 18 patients with lung cancer, CANDIN® elicited a positive induration response in five patients (28%). In a second series of 20 patients with metastatic cancer, no reactions ≥5 mm were observed (Table 3).

Table 3. Cellular Hypersensitivity Response to CANDIN® in adults with Cancer.

 | n | Age; Range; (years) | Number; reactions; ≥ 5mm at; 48 hours | Response
Study 1 | 18 | 52-75 | 5 | 28%
Study 2 | 20 | 47-81 | 0 | 0%

15 REFERENCES

1. Middleton, E. Jr., Reed, C.E., Ellis, F.E., Adkinson, N.F., Jr., Yunginger, J.W., Busse, W.W., Allergy Principles and Practice, 5th Ed., Vol II, pp 685-687, Mosby, St. Louis, 1998.
2. Bernstein, I.L., ed., Proceedings of the task force of guidelines for standardizing old and new technologies used for the diagnosis and treatment of allergy, J. Allergy Clin. Immunol., 82: 487-526, 1988.
3. Paul, W.E., Fundamental Immunology, 3rd Ed., pp 75-76, Raven Press, New York, 1993.
4. MacPhee, M.J., Gordon, J., Christou, N.V., Sanchez-Cantu, L., Rode, H.H., Cells recovered from human DTH reactions: phenotypic and functional analysis. Cellular Immunology, 151: 80-96, 1993.
5. CDC, 1993 revised classification system for HIV infection and expanded surveillance case definition for AIDS among adolescents and adults. Morbidity and Mortality Weekly Report. 41: No. RR17, December 18, 1992.
6. Huebner, R.E., Schein, M.F., Hall, C.A., Barnes, S.A., Delayed-type hypersensitivity anergy in human immunodeficiency virus-infected persons screened for infection with Mycobacterium tuberculosis. Clin. Infect. Dis., 19: 26-32, 1994.
7. Klotz, S.D., Sweeney, M.J., Dienst, S., Klotz, L.R., Moeller, R.K., Rosenberg, S., Systemic anaphylaxis immediately following delayed hypersensitivity skin tests. Ann. Allergy, 49: 142-144, 1982.

16 HOW SUPPLIED/STORAGE AND HANDLING

CANDIN® is supplied in a 1 mL multidose vial containing ten 0.1 mL doses.

Storage

Store between 2 - 8°C. Do not freeze.

17 PATIENT COUNSELING INFORMATION

Local reactions to CANDIN® can include redness, swelling, pruritus, excoriation and discoloration of the skin. These reactions usually subside within hours or days after administration of the skin test. In some patients, skin discoloration may persist for several weeks. Progression of the DTH reaction to vesiculation, necrosis and ulceration are possible. Patients should be informed that all foreign antigens have the remote possibility of causing Type I anaphylactic reactions that may require the administration of epinephrine and other drugs or emergency procedures and may be life threatening in some cases. Patients should report any serious adverse reactions to their health care provider.

*Sections or subsections omitted from the full prescribing information are not listed.

CA-C Circular Date of Issue: September 27, 2021

Nielsen BioSciences, Inc.
11125 Flintkote Avenue Suite G
San Diego, CA 92121
(855) 855-1212
www.nielsenbio.com

Candida albicans Skin Test Antigen
for Cellular Hypersensitivity
CANDIN®

Mfg. by Allermed Laboratories, Inc.
San Diego, CA. 92111

NDC 59584-138-01 - Vial Label

NDC 59584-138-01

Candida albicans Skin Test Antigen for Cellular Hypersensitivity

Candin®

Mfd. for Nielsen BioSciences, Inc.

San Diego CA 92121

Vol: 1mL (10 Tests)

Dose: 0.1mL Intradermally

See Package Insert

Store: 2-8°C Rx Only

Preservatives: 0.4% Phenol

Lot:

Exp:

NDC 59584-138-01 - Carton Label

Candida albicans Skin Test Antigen

for Cellular Hypersensitivity

Candin®

Skin Test Strength

For use in assessing cell-mediated or delayed-type hypersensitivity to Candida albicans.

Mfd. for Nielsen BioSciences, Inc. U.S. License 1903

San Diego, CA 92121

Dose: 0.1 mL intradermally. See circular.

Contents: 1 mL multidose vial (ten tests).

Ingredients: Candida antigen in buffered saline with 0.03% albumin USP, 8 ppm polysorbate 80 and phenol 0.4% w/v as a preservative.

Rev. 08/21

Potency: Measured by delayed-type intradermal skin test in guinea pigs.

Storage: Store at 2-8° C (35-46° F). Do not freeze.

No U.S. Standard of Potency.

Rx only.

NDC 59584-138-01